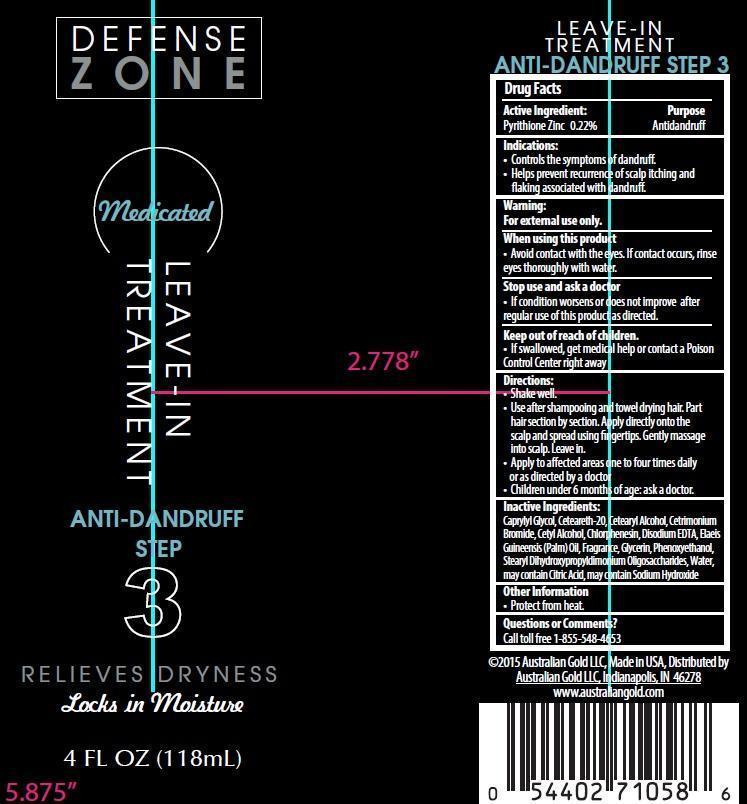 DRUG LABEL: Australian Gold Defense Zone
NDC: 58443-0184 | Form: LOTION
Manufacturer: Prime Enterprises, Inc.
Category: otc | Type: HUMAN OTC DRUG LABEL
Date: 20200117

ACTIVE INGREDIENTS: PYRITHIONE ZINC 2.14 mg/1 mL
INACTIVE INGREDIENTS: CAPRYLYL GLYCOL; POLYOXYL 20 CETOSTEARYL ETHER; CETOSTEARYL ALCOHOL; CETYL ALCOHOL; CETRIMONIUM BROMIDE; CHLORPHENESIN; CITRIC ACID MONOHYDRATE; EDETATE DISODIUM; PALM OIL; GLYCERIN; PHENOXYETHANOL; SODIUM HYDROXIDE; GUAR HYDROXYPROPYLTRIMONIUM CHLORIDE (1.7 SUBSTITUENTS PER SACCHARIDE); WATER

Active ingredient:

Pyrithione Zinc 0.22%

Purpose

Antidanruff

Indications:

- Controls the symptoms of dandruff.
- Helps prevent recurrence of scalp itching and flaking associated with dandruff.

Warning:

OTHER SAFETY INFORMATION

For external use only.

When using this product

- Avoid contact with the eyes. If contact occurs, rinse eyes thorougly with water.

Stop use and ask a doctor

- If condition worsens or does not improve after regular use of this product as directed.

Keep out of reach of children.

- If swallowed, get medical help or contact a Poison Control Center right away

Directions:

- Shake well.
- Use after shampooing and towel drying hair. Part hair section by section. Apply directly onto the scalp and spread using fingertips. Gently massage into scalp. Leave in.
- Apply to affected areas one to four times daily or as directed by a doctor
- Children under 6 months of age: ask a doctor.

Inactive Ingrediets:

Caprylyl Glycol, Ceteareth-20, Cetearyl Alcohol, Cetrimonium Bromide, Cetyl Alcohol, Chlorphenesin, Citric Acid, Disodium EDTA, Elaeis Guineensis (Palm) Oil, Fragrance, Glycerin, Phenoxyethanol, Sodium Hydroxide, Stearyl Dihydroxypropyldisodium Oligosaccharides, Water

Questions or Comments?

Call toll free 1-855-548-4653

PRINCIPAL DISPLAY PANEL - 118 mL Bottle Label

Defense

Zone

Medicated

LEAVE-IN

TREATMENT

Anti-Dandruff

Step

3

Relieves Dryness

Locks in Moisture

4 FL OZ (118mL)